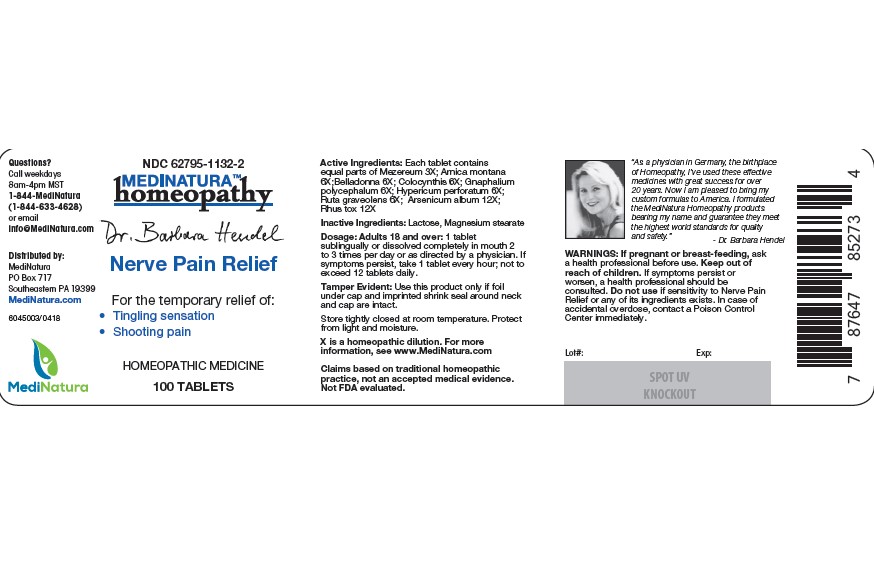 DRUG LABEL: Hendel Nerve Pain Relief
NDC: 62795-1132 | Form: TABLET
Manufacturer: MediNatura Inc
Category: homeopathic | Type: HUMAN OTC DRUG LABEL
Date: 20230216

ACTIVE INGREDIENTS: DAPHNE MEZEREUM BARK 3 [hp_X]/1 1; ARNICA MONTANA 6 [hp_X]/1 1; ARSENIC TRIOXIDE 12 [hp_X]/1 1; ATROPA BELLADONNA 6 [hp_X]/1 1; TOXICODENDRON PUBESCENS LEAF 6 [hp_X]/1 1; CITRULLUS COLOCYNTHIS FRUIT PULP 6 [hp_X]/1 1; PSEUDOGNAPHALIUM OBTUSIFOLIUM 6 [hp_X]/1 1; HYPERICUM PERFORATUM 6 [hp_X]/1 1; RUTA GRAVEOLENS FLOWERING TOP 6 [hp_X]/1 1
INACTIVE INGREDIENTS: MAGNESIUM STEARATE; LACTOSE MONOHYDRATE

Hendel Nerve Pain Relief

WARNINGS

If pregnant or breast-feeding, ask a health professional before use. Keep out of reach of children. If symptoms persist or worsen, a health professional should be consulted. Do not use if sensitivity to Nerve Pain Relief or any of its ingredients exists. In case of accidental overdose, contact a Poison Control Center immediately.

KEEP OUT OF REACH OF CHILDREN

PURPOSE

Nerve Pain Relief

INGREDIENTS

Each tablet contains equal parts of Mezereum 3X; Arnica montana 6X; Arsenicum album 12X; Belladonna 6X; Colocynthis 6X; Gnaphalium polycephalum 6X; Hypericum perforatum 6X; Ruta graveolens 6X; Rhux tox 12X

INACTIVE INGREDIENT

Lactose, Magnesium stearate

DIRECTIONS

Adults 18 and over: 1 tablet sublingually or dissolved completely in mouth 2 to 3 times per day or as directed by a physician. If symptoms persist, take 1 tablet every hour; not to exceed 12 tablets daily.

USES

For the temporary relief of:
• Tingling sensation
• Shooting pain

PACKAGE LABEL

Add image transcription here...